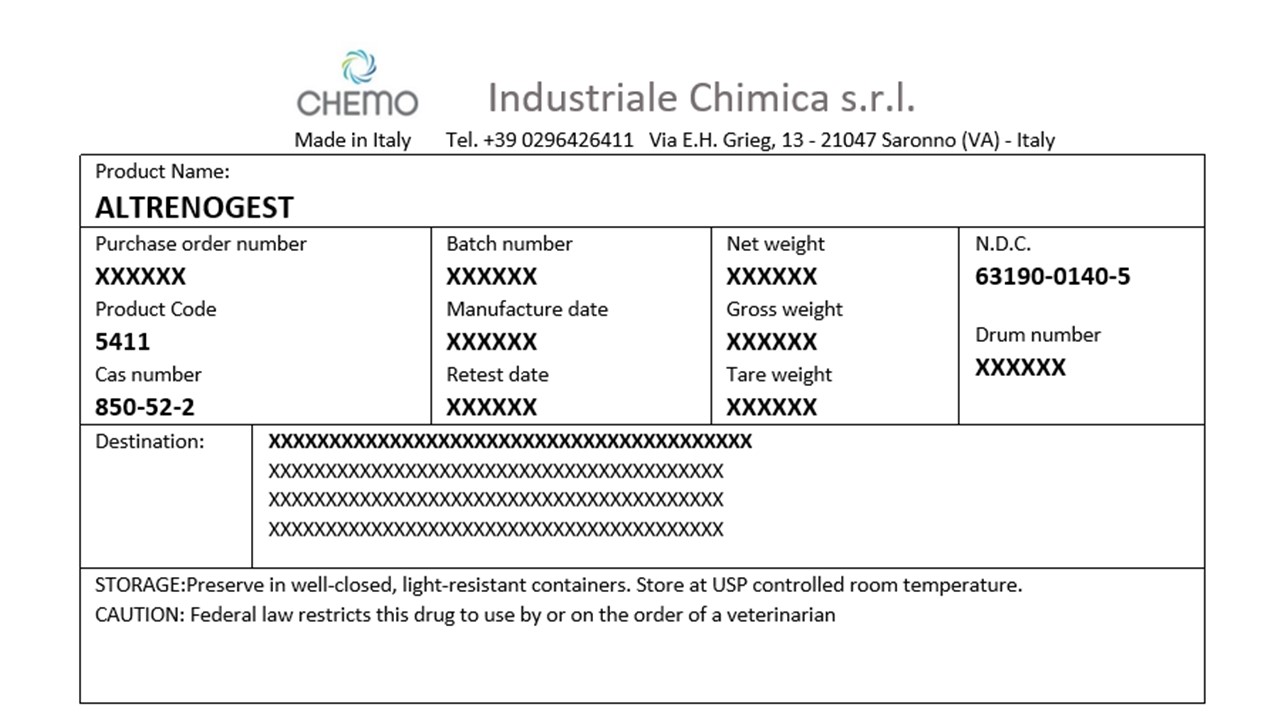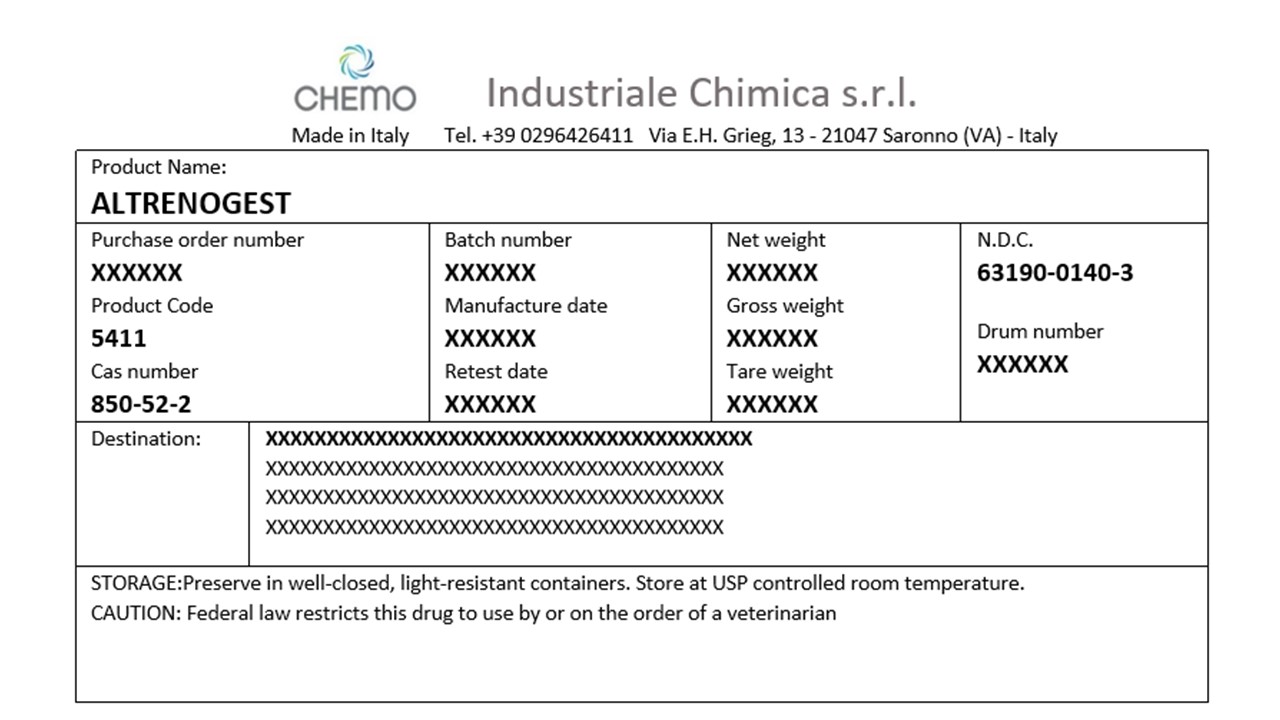 DRUG LABEL: Altrenogest
NDC: 63190-0140 | Form: POWDER
Manufacturer: Industriale Chimica s.r.l.
Category: other | Type: BULK INGREDIENT - ANIMAL DRUG
Date: 20221216

ACTIVE INGREDIENTS: ALTRENOGEST 1 kg/1 kg

PACKAGE LABEL

Altrenogest